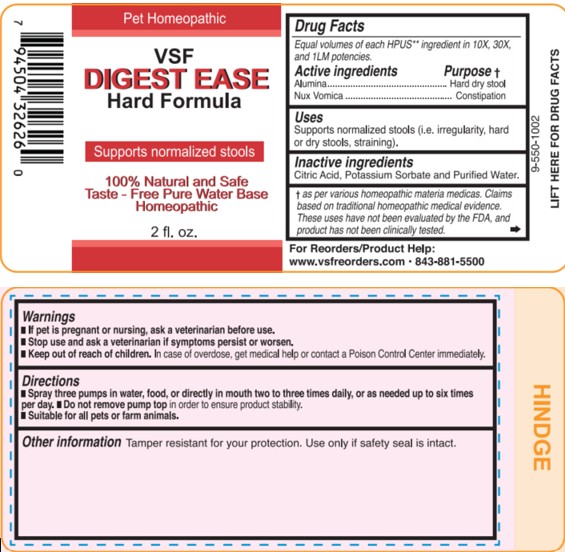 DRUG LABEL: Digest Ease Hard Formula
NDC: 86100-0012 | Form: LIQUID
Manufacturer: Vsf2 Inc.
Category: homeopathic | Type: OTC ANIMAL DRUG LABEL
Date: 20250825

ACTIVE INGREDIENTS: ALUMINUM OXIDE 10 [hp_X]/59 mL; STRYCHNOS NUX-VOMICA SEED 10 [hp_X]/59 mL
INACTIVE INGREDIENTS: ANHYDROUS CITRIC ACID; POTASSIUM SORBATE; WATER

Digest Ease Hard Formula

Active ingredients

Equal volumes of each HPUS** ingredient in 10X,
30X, and 1LM potencies.

Alumina and Nux vomica.

Uses

Supports normalized stools (i.e. irregularity, hard or dry stools, straining).

† as per various homeopathic materia medicas. Claims based on traditional homeopathic medical evidence.
These uses have not been evaluated by the FDA, and product has not been clinically tested

Other information

Tamper resistant for your protection.

Use only if safety seal is intact.

100% Natural and Safe Taste

Free Pure Water Base Homeopathic

For Reorders/Product Help:

wwwvsfreorders.com 843-881-5500

Warnings

- If pet is pregnant or nursing, ask a veterinarian before use.
- Stop use and ask a veterinarian if symptoms persist or worsen.
- Keep out of reach of children. In case of overdose, get medical help or contact a Poison Control Center immediately.

Keep out of reach of children. In case of overdose, get medical help or contact a Poison Control Center immediately.

DOSAGE AND ADMINISTRATION

- Spray three pumps in water, food, or directly in mouth two to three times daily, or as needed up to six times per day.

- Do not remove pump top in order to ensure product stability.

- Suitable for all pets or farm animals.

Other information

Tamper resistant for your protection. Use only if safety seal is intact.

Inactive Ingredients

Citric Acid, Potassium Sorbate, and Purified Water.

PURPOSE

Equal volumes of each HPUS** ingredient in 10X,
30X, and 1LM potencies.

Active ingredients Purpose †

Alumina....................................Hard dry stool

Nux vomica.................................Constipation

† as per various homeopathic materia medicas. Claims based on traditional homeopathic medical evidence.
These uses have not been evaluated by the FDA, and product has not been clinically tested.